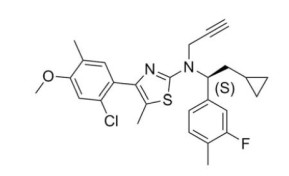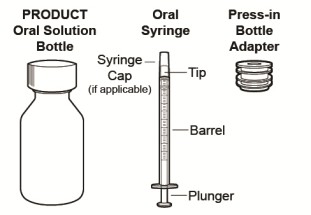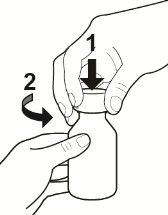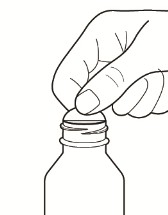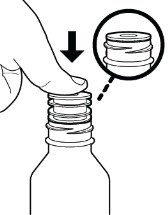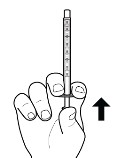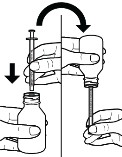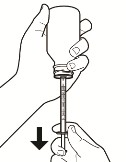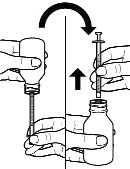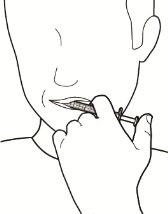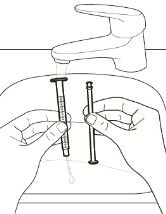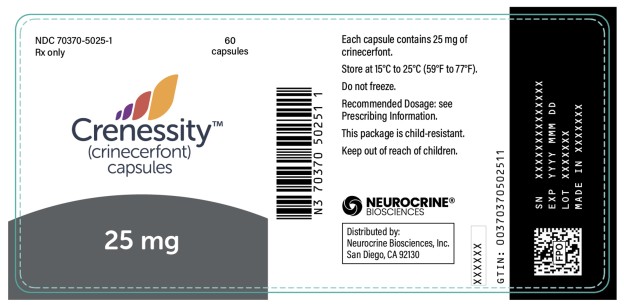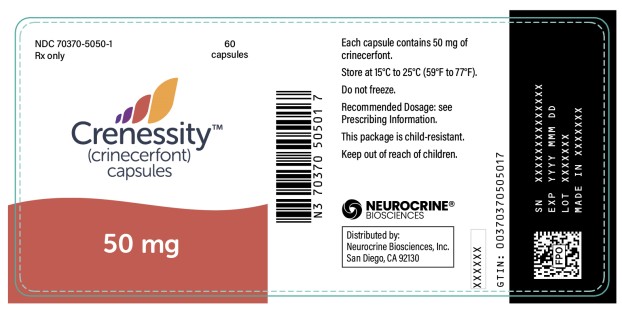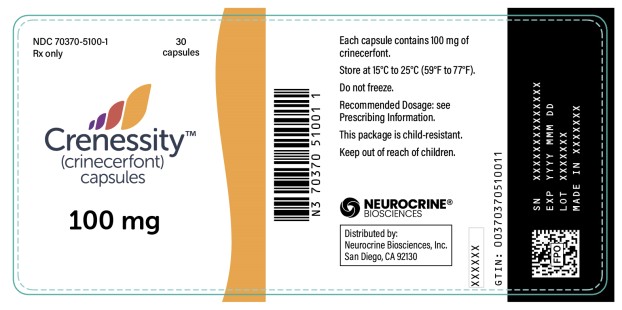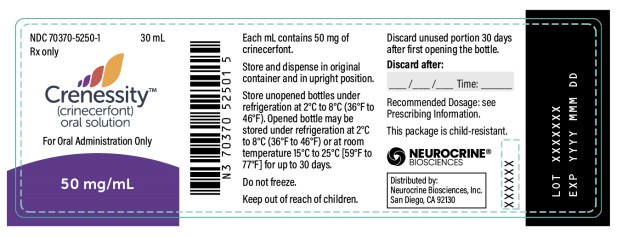 DRUG LABEL: Crenessity
NDC: 70370-5025 | Form: CAPSULE
Manufacturer: Neurocrine Biosciences, Inc.
Category: prescription | Type: HUMAN PRESCRIPTION DRUG LABEL
Date: 20241210

ACTIVE INGREDIENTS: CRINECERFONT 25 mg/1 1
INACTIVE INGREDIENTS: LAUROYL PEG-32 GLYCERIDES; PROPYLENE GLYCOL DICAPRYLATE/DICAPRATE; MEDIUM-CHAIN TRIGLYCERIDES; VITAMIN E POLYETHYLENE GLYCOL SUCCINATE; GELATIN; SORBITOL; TITANIUM DIOXIDE; FERRIC OXIDE RED; FERRIC OXIDE YELLOW; GLYCERIN; WATER

HIGHLIGHTS OF PRESCRIBING INFORMATION

These highlights do not include all the information needed to use CRENESSITY safely and effectively. See full prescribing information for CRENESSITY.
CRENESSITY™ (crinecerfont) capsules, for oral use
CRENESSITY™ (crinecerfont) oral solution
Initial U.S. Approval: 2024

1 INDICATIONS AND USAGE

CRENESSITY is a corticotropin-releasing factor type 1 receptor antagonist indicated as adjunctive treatment to glucocorticoid replacement to control androgens in adults and pediatric patients 4 years of age and older with classic congenital adrenal hyperplasia (CAH).

2 DOSAGE AND ADMINISTRATION

- Continue glucocorticoid replacement therapy for adrenal insufficiency associated with CAH. (2.1)
- Adults: 100 mg orally, twice daily with a meal in the morning and evening. (2.2)
- Pediatric Patients (4 years of age and older): Weight-based dosage orally, twice daily with a meal in the morning and evening. (2.2)
- See Full Prescribing Information for complete dosage and administration information.

3 DOSAGE FORMS AND STRENGTHS

- Capsules: 25 mg, 50 mg, 100 mg (3)
- Oral Solution: 50 mg/mL (3)

4 CONTRAINDICATIONS

Hypersensitivity to crinecerfont or any excipients of CRENESSITY. (4)

5 WARNINGS AND PRECAUTIONS

- Hypersensitivity Reactions: Include throat tightness, angioedema, and generalized rash. If clinically significant hypersensitivity occurs, initiate appropriate therapy and discontinue CRENESSITY. (5.1)
- Risk of Acute Adrenal Insufficiency or Adrenal Crisis with Inadequate Concomitant Glucocorticoid Therapy: Continue glucocorticoids upon initiation of and during treatment with CRENESSITY. Do not reduce the glucocorticoid dose below the dose required for cortisol replacement. Any adjustment of daily glucocorticoid dosage after initiation of CRENESSITY should be performed under the supervision of a health care provider. Use glucocorticoid stress doses in cases of increased cortisol need (e.g., acute intercurrent illness, serious trauma, surgical procedures). (5.2)

6 ADVERSE REACTIONS

Adults: Most common adverse reactions (at least 4% for CRENESSITY and greater than placebo) are fatigue, headache, dizziness, arthralgia, back pain, decreased appetite, and myalgia. (6.1)

Pediatric Patients: Most common adverse reactions (at least 4% for CRENESSITY and greater than placebo) are headache, abdominal pain, fatigue, nasal congestion, and epistaxis. (6.1)

To report SUSPECTED ADVERSE REACTIONS, contact Neurocrine Biosciences, Inc. at 877-641-3461 or FDA at 1-800-FDA-1088 or www.fda.gov/medwatch.

7 DRUG INTERACTIONS

Strong CYP3A4 Inducers: Increase CRENESSITY morning and evening dosage 2-fold. (Section 2.3, 7.1)

Moderate CYP3A4 Inducers: Increase CRENESSITY evening dosage 2-fold. (2.4, 7.1)

FULL PRESCRIBING INFORMATION

1 INDICATIONS AND USAGE

CRENESSITY is indicated as adjunctive treatment to glucocorticoid replacement to control androgens in adults and pediatric patients 4 years of age and older with classic congenital adrenal hyperplasia (CAH).

2 DOSAGE AND ADMINISTRATION

2.1 Important Administration Information

Patients receiving CRENESSITY should continue glucocorticoid replacement therapy for the adrenal insufficiency associated with congenital adrenal hyperplasia (see Warning and Precautions (5.2).

Androstenedione levels can be assessed beginning four weeks after CRENESSITY initiation to inform reduction in glucocorticoid dosage as clinically indicated. Do not reduce the glucocorticoid dosage below that required for replacement therapy.

2.2 Recommended Dosage and Administration

Recommended Dosage for Adults

The recommended CRENESSITY dosage for adults is 100 mg orally, twice daily with a meal in the morning and evening [see Clinical Pharmacology (12.3)].

Recommended Dosage for Pediatric Patients 4 Years of Age and Older

The recommended CRENESSITY dosage for pediatric patients 4 years of age and older is weight-based and administered orally, twice daily with a meal in the morning and evening (see Table 1) [see Clinical Pharmacology (12.3)].

Table 1: Recommended CRENESSITY Weight-Based Dosage for Pediatric Patients 4 Years of Age and Older

Weight | Dosage Regimen with a Meal
10 kg to less than 20 kg | 25 mg orally twice daily
20 kg to less than 55 kg | 50 mg orally twice daily
Greater than or equal to 55 kg | 100 mg orally twice daily

2.3 Dosage Modifications for Concomitant Use with Strong CYP3A4 Inducers

Adults

In adults, increase the CRENESSITY dosage to 200 mg orally, twice daily with a meal in the morning and evening when used concomitantly with strong CYP3A4 inducers [see Drug Interactions (7.1)].

Pediatric Patients 4 Years of Age and Older

In pediatric patients, increase the CRENESSITY dosage with a meal in the morning and evening when used concomitantly with strong CYP3A4 inducers as shown in Table 2 [see Drug Interactions (7.1)].

Table 2: Dosage Increase of CRENESSITY for Use with Strong CYP3A4 Inducers in Pediatric Patients 4 Years of Age and Older

Weight | Dosage Regimen with a Meal
10 kg to less than 20 kg | 50 mg orally twice daily
20 kg to less than 55 kg | 100 mg orally twice daily
Greater than or equal to <55 kg | 200 mg orally twice daily

2.4 Dosage Modifications for Concomitant Use with Moderate CYP3A4 Inducers

Adults

In adults, increase the CRENESSITY dosage to 200 mg orally with the evening meal when used concomitantly with moderate CYP3A4 inducers. The CRENESSITY dosage of 100 mg with the morning meal remains unchanged [see Drug Interactions (7.1)].

Pediatric Patients 4 Years of Age and Older

In pediatric patients, increase the CRENESSITY dosage with the evening meal when used concomitantly with moderate CYP3A4 inducers as shown in Table 3 [see Drug Interactions (7.1)].

Table 3. Dosage Increase of CRENESSITY for Use with Moderate CYP3A4 Inducers in Pediatric Patients 4 Years of Age and Older

 | Dosage Regimen with a Meal
Weight | Morning Dose | Evening Dose
10 kg to less than 20 kg | 25 mg orally | 50 mg orally
20 kg to less than 55 kg | 50 mg orally | 100 mg orally
Greater than or equal to 55 kg | 100 mg orally | 200 mg orally

2.5 Administration Instructions

Administer CRENESSITY orally, twice daily, with a meal in the morning and evening [see Clinical Pharmacology (12.3)].

CRENESSITY Capsules

Take CRENESSITY capsules orally and swallow whole with liquid.

CRENESSITY Oral Solution

Refer patients and/or caregivers to the Instructions for Use (IFU) for complete administration instructions.

Discard any unused CRENESSITY oral solution after 30 days of first opening the bottle [see How Supplied/Storage and Handling (16.2)].

2.6 Missed Doses

If a dose or doses are missed, advise the patient to take one dose of CRENESSITY as soon as possible (even if it is soon before the next scheduled dose) and then to resume the regular dosing schedule.

3 DOSAGE FORMS AND STRENGTHS

CRENESSITY is available as:

- Capsules
  - 25 mg oval, orange soft gelatin capsule printed with ‘WWV 25’ in black ink
  - 50 mg oval, two-toned orange and gold soft gelatin capsule printed with ‘WWV 50’ in black ink
  - 100 mg oblong, gold soft gelatin capsule printed with ‘WWV 100’ in black ink
- Oral Solution: 50 mg/mL in light yellow to orange, clear to slightly opalescent oral solution

4 CONTRAINDICATIONS

CRENESSITY is contraindicated in patients with hypersensitivity to crinecerfont or any excipients of CRENESSITY. Reactions have included throat tightness, angioedema, and generalized rash [see Warnings and Precautions (5.1)].

5 WARNINGS AND PRECAUTIONS

5.1 Hypersensitivity Reactions

A hypersensitivity reaction, including throat tightness, angioedema, and generalized rash, occurred in a subject after 3 days of treatment with CRENESSITY.

If a clinically significant hypersensitivity reaction occurs, initiate appropriate therapy and discontinue CRENESSITY.

5.2 Risk of Acute Adrenal Insufficiency or Adrenal Crisis with Inadequate Concomitant Glucocorticoid Therapy

Continue glucocorticoids upon initiation of and during treatment with CRENESSITY. Do not reduce the glucocorticoid dose below the dose required for cortisol replacement.

Acute adrenal insufficiency or adrenal crisis, which can potentially be fatal or life-threatening, can occur in patients with underlying adrenal insufficiency who are on inadequate daily glucocorticoid doses, especially in situations associated with increased cortisol need, such as acute intercurrent illness, serious trauma, or surgical procedures.

Any adjustment of daily glucocorticoid dosage after initiation of CRENESSITY should be performed under the supervision of a health care provider. Use glucocorticoid stress doses in case of increased cortisol need (e.g., acute intercurrent illness, serious trauma, surgical procedures).

In the placebo-controlled clinical study of adults with classic CAH, the incidence of adrenal crisis was 1.6% in subjects treated with CRENESSITY and 0% in subjects treated with placebo. In the placebo-controlled clinical study of pediatric subjects with classic CAH, there were no events of adrenal crisis.

6 ADVERSE REACTIONS

The following clinically significant adverse reactions are described elsewhere in the labeling:

- Hypersensitivity Reactions [see Warnings and Precautions (5.1)]
- Risk of Acute Adrenal Insufficiency or Adrenal Crisis with Inadequate Concomitant Glucocorticoid Therapy [see Warnings and Precautions (5.2)]

6.1 Clinical Trials Experience

Because clinical trials are conducted under widely varying conditions, adverse reaction rates observed in the clinical trials of a drug cannot be directly compared to rates in the clinical trials of another drug and may not reflect the rates observed in practice.

Adults with Congenital Adrenal Hyperplasia (CAH)

The safety of CRENESSITY in adults was assessed in Study 1, a randomized, double-blind, placebo-controlled study of 182 adults aged 18 to 58 years with classic CAH due to 21-hydroxylase deficiency. A total of 122 subjects received CRENESSITY 100 mg twice daily and 59 subjects received placebo twice daily for up to 24 weeks [see Clinical Studies (14.1)].

Adverse Reactions Leading to Discontinuation of Treatment

A total of 3% of CRENESSITY-treated subjects and no placebo-treated subjects discontinued treatment because of adverse reactions of restlessness, apathy, dyspepsia, nausea, and vomiting.

Commonly Observed Adverse Reactions

Adverse reactions that occurred in ≥4% of CRENESSITY-treated subjects and more frequently than in placebo-treated subjects are presented in Table 4.

Table 4: Adverse Reactions (≥4%) in Adults with Congenital Adrenal Hyperplasia Treated with CRENESSITY and Occurring More Frequently Than in Placebo-Treated Subjects

Adverse Reactions | CRENESSITY (N=122) % | Placebo (N=59) %
Fatigue | 25 | 15
Headache | 16 | 15
Dizziness | 8 | 3
Arthralgia | 7 | 0
Back pain | 6 | 3
Decreased appetite | 4 | 2
Myalgia | 4 | 3

Suicidal Ideation and Behavior

Study 1 excluded subjects with active suicidal ideation with intent or plan within the six months prior to screening and those with a history of suicidal behavior within the past year, based on the Columbia-Suicide Severity Rating Scale (C-SSRS) administered at screening. The C-SSRS was administered to subjects at regular intervals during the study. Three of 122 (2.5%) CRENESSITY-treated subjects reported suicidal ideation without method, intent or plan on the C-SSRS during the 24-week double-blind treatment period compared to 1 of 59 (1.7%) placebo-treated subjects. One of the three subjects receiving CRENESSITY and the placebo-treated subject reported a lifetime history of suicidal ideation.

One CRENESSITY-treated subject without a history of suicidal ideation or behavior attempted suicide during the open-label period after 320 days of treatment.

Laboratory Findings

Neutrophil count less than 2 x 10^3 cells/mcL occurred in 14% (17 of 120) of CRENESSITY-treated subjects, compared to 5% (3 of 58) of subjects in the placebo group. Neutrophil count less than 1 x 10^3 cells/mcL occurred in 0.8% (1 of 120) of CRENESSITY-treated subjects, compared to 1.7% subjects (1 of 58) in the placebo group.

Pediatric Patients with Congenital Adrenal Hyperplasia

The safety of CRENESSITY in pediatric patients was evaluated in Study 2, a randomized, double-blind placebo-controlled study of 103 pediatric subjects aged 4 to 17 years with classic CAH due to 21-hydroxylase deficiency. Pediatric subjects were randomized to receive CRENESSITY twice daily (N=69) or placebo (N=34) for 28 weeks, using weight-based dosing (50 mg twice daily via oral solution for subjects 20 to <55 kg, or 100 mg twice daily via oral capsules for subjects ≥55 kg) [see Clinical Studies (14.2)].

Adverse Reactions Leading to Discontinuation of Treatment

A total of 3% of CRENESSITY-treated subjects and no placebo-treated subjects discontinued treatment because of adverse reactions of abdominal pain, myalgia, and dizziness.

Commonly Observed Adverse Reactions

Adverse reactions that occurred at an incidence of ≥4% in CRENESSITY-treated pediatric subjects (50 mg twice daily or 100 mg twice daily) and greater than placebo are presented in Table 5.

Table 5: Adverse Reactions (≥ 4%) in Pediatric Subjects with Congenital Adrenal Hyperplasia Treated with CRENESSITY and Occurring More Frequently Than in Placebo-Treated Subjects

Adverse Reactions | CRENESSITY (N=69) % | Placebo (N=33) %
Headache | 25 | 6
Abdominal pain^1 | 13 | 0
Fatigue | 7 | 0
Nasal congestion | 7 | 3
Epistaxis | 4 | 0

^1Abdominal pain includes: abdominal pain, abdominal pain upper and abdominal pain lower

Suicidal Ideation and Behavior

Study 2 excluded subjects with active suicidal ideation with intent or plan within six months prior to screening or those with a lifetime history of suicidal behavior based on the C-SSRS administered at screening. Four of 67 (6%) CRENESSITY-treated subjects and 0 of the 31 (0%) placebo-treated subjects reported suicidal ideation without method, intent or plan on the C-SSRS during the 28-week double-blind treatment period. Two of the four CRENESSITY-treated subjects reported a lifetime history of suicidal ideation. There were no completed suicides or suicide attempts.

Laboratory Findings

Neutrophil count less than 2 x 10^3 cells/mcL occurred in 37% (25 of 68) of CRENESSITY-treated subjects, compared to 16% (5 of 32) of subjects in the placebo group. Neutrophil count less than 1 x 10^3 cells/mcL occurred in 4% (3 of 68) of CRENESSITY-treated subjects, compared to no subjects (0 of 32) in the placebo group.

7 DRUG INTERACTIONS

7.1 Effects of Other Drugs on CRENESSITY

Strong CYP3A4 Inducers

Increase CRENESSITY morning and evening dosages 2-fold when CRENESSITY is used concomitantly with a strong CYP3A4 inducer [see Dosage and Administration (2.3)].

Moderate CYP3A4 Inducers

Increase CRENESSITY evening dosage 2-fold when CRENESSITY is used concomitantly with a moderate CYP3A4 inducer. Do not increase the morning dosage [see Dosage and Administration (2.4)].

Mechanism of Drug Interaction and Clinical Effect

CRENESSITY is a CYP3A4 substrate. Concomitant use of CRENESSITY with a strong or moderate CYP3A4 inducer decreases crinecerfont exposure [see Clinical Pharmacology (12.3)], which may reduce CRENESSITY efficacy.

8 USE IN SPECIFIC POPULATIONS

8.1 Pregnancy

Risk Summary

Available data from reports of pregnancy in clinical trials with CRENESSITY are insufficient to identify a drug-associated risk of major birth defects, miscarriage or other adverse maternal or fetal outcomes.

No developmental toxicity was observed in rats at 4-fold higher than human exposure at the maximum recommended human dose (MRHD) based on area under the concentration-time curve (AUC). Crinecerfont was associated with a low incidence of poly-malformations (craniofacial defects) in rabbits at 2-fold higher than human exposure at the MRHD. In a pre- and postnatal developmental toxicity study, no developmental toxicity was observed in rats at 4-fold higher than human exposure at the MRHD (see Data).

The background risk of major birth defects and miscarriage for the indicated population is unknown. All pregnancies have a background risk of birth defect, loss, or other adverse outcomes. In the U.S. general population, the estimated background risk of major birth defects and miscarriage in clinically recognized pregnancies is 2% to 4% and 15% to 20%, respectively.

If CRENESSITY is administered during pregnancy, or if a patient becomes pregnant while receiving CRENESSITY, health care providers should report exposure to CRENESSITY by calling 1-855-CRNSITY (1-855-276-7489).

Data

Animal Data

Crinecerfont was administered orally to pregnant rabbits at doses of 100, 500, and 1000 mg/kg/day, and to pregnant rats at doses of 150, 500, and 2000 mg/kg/day during the period of organogenesis. No crinecerfont-related malformations were observed in rats at 4-fold higher than human exposure at the MRHD based on AUC. Low incidence of poly-malformations (craniofacial defects) and slightly lower mean fetal weights were observed in rabbits treated with crinecerfont at 2-fold higher than human exposure at the MRHD based on AUC.

In a pre- and postnatal developmental toxicity study, crinecerfont was administered orally to pregnant rats at doses of 15, 50, and 250 mg/kg/day during the period of organogenesis and lactation through Day 20 postpartum. No changes in pup mortality, growth, sexual maturation, behavior, mating and fertility, or ovarian and uterine parameters were observed. The exposure in dams at the No Observed Adverse Effect Level (NOAEL) of 250 mg/kg/day was approximately 4-fold higher than human exposure at the MRHD based on AUC.

8.2 Lactation

Risk Summary

There are no data on the presence of crinecerfont in human milk, the effects on the breastfed infant, or the effects on milk production. Crinecerfont is present in animal milk. (see Data). When a drug is present in animal milk, it is likely that the drug will be present in human milk. Infants exposed to CRENESSITY through breast milk should be monitored for signs of adrenal insufficiency such as weakness, decreased feeding and weight loss.

The developmental and health benefits of breastfeeding should be considered along with the mother’s clinical need for CRENESSITY and any potential adverse effects on the breastfed child from CRENESSITY or from the underlying maternal condition.

Data

Crinecerfont was excreted in the milk of rats, with milk-to-plasma concentration ratios ranging from 1.5 to 12. No effects on postnatal development were observed in a pre- and postnatal development study, in which female rats were treated orally with up to 250 mg/kg/day (4-fold higher than human exposure at the MRHD based on AUC) during organogenesis through lactation.

8.4 Pediatric Use

The safety and effectiveness of CRENESSITY as adjunctive treatment to glucocorticoid replacement to control androgens have been established in pediatric patients 4 years of age and older with classic CAH. Use of CRENESSITY for this indication is supported by evidence from an adequate and well-controlled study of 103 pediatric subjects (Study 2), evidence from an adequate and well-controlled study in adults with CAH (Study 1), and pharmacokinetic data from adults and pediatric subjects [see Dosage and Administration (2.2), Warnings and Precautions (5.2), Adverse Reactions (6.1), Clinical Pharmacology (12.3), and Clinical Studies (14.2)].

The safety and effectiveness of CRENESSITY in pediatric patients less than 4 years of age have not been established.

8.5 Geriatric Use

The clinical trial of CRENESSITY in adults with classic CAH did not enroll subjects 65 years of age and older to determine whether they respond differently from younger subjects.

8.6 Renal Impairment

CRENESSITY is not recommended in patients with severe renal impairment or end-stage renal disease [see Clinical Pharmacology (12.3)].

11 DESCRIPTION

CRENESSITY contains crinecerfont, a selective corticotropin-releasing factor type 1 receptor antagonist, present as crinecerfont free base, with the chemical name, 2-thiazolamine, 4-(2-chloro-4-methoxy-5-methylphenyl)-N-[(1S)-2-cyclopropyl-1-(3-fluoro-4-methylphenyl)ethyl]-5-methyl-N-2-propyn-1-yl. Crinecerfont free base is the S-enantiomer with an enantiomeric excess of at least 99.7%. Its molecular formula is C27H28ClFN2OS, and its molecular weight is 483.04 g/mol with the following structure:

CRENESSITY Capsules

CRENESSITY capsules are intended for oral administration only. Each capsule contains 25 mg, 50 mg, or 100 mg of crinecerfont free base. Inactive ingredients include lauroyl polyoxyl-32 glycerides, medium chain triglycerides, propylene glycol dicaprylate/dicaprate, and Vitamin E polyethylene glycol succinate. The capsule shell contains gelatin, glycerin, red iron oxide, Sorbitol glycerin blend, titanium dioxide, and yellow iron oxide.

CRENESSITY Oral Solution

The oral solution formulation contains 50 mg/mL of crinecerfont free base. Inactive ingredients include butylated hydroxytoluene, medium-chain triglycerides, oleoyl polyoxyl glycerides, orange flavor, and saccharin.

12 CLINICAL PHARMACOLOGY

12.1 Mechanism of Action

Crinecerfont is a selective corticotropin-releasing factor (CRF) type 1 receptor antagonist. Crinecerfont blocks the binding of CRF to CRF type 1 receptors in the pituitary but not CRF type 2 receptors. Crinecerfont binding to CRF type 1 receptors inhibits adrenocorticotropic hormone (ACTH) secretion from the pituitary, thereby reducing ACTH-mediated adrenal androgen production.

12.2 Pharmacodynamics

Exposure-Response Relationships

Model based exposure-response analyses for adults and pediatric patients with CAH demonstrated that, within the studied exposures of CRENESSITY in Phase 3 trials, relatively flat exposure-response relationships were observed for androstenedione reduction from baseline to Week 4 for both adults and pediatric patients and percent glucocorticoid daily dose reduction from baseline to Week 24 for adults and to Week 28 for pediatric patients.

Adrenocorticotropic Hormone (ACTH) Reduction

In 8 adults with classic CAH (NCT0352886) who received the recommended CRENESSITY dosage for 2 weeks, the median percent reduction from baseline in ACTH was 62%.

In the Phase 3 clinical trials of adults and pediatric patients with classic CAH, administration of the recommended CRENESSITY dosage for 4 weeks during the initial glucocorticoid stable period led to a reduction in ACTH levels.

In Study 1, the median percent reduction from baseline to Week 4 in ACTH was 65%.

In Study 2, the median percent reduction from baseline to Week 4 in ACTH was 72%.

Cardiac Electrophysiology

At a dose 4 times the maximum approved recommended dosage, CRENESSITY does not prolong the QT interval to any clinically relevant extent.

12.3 Pharmacokinetics

Crinecerfont maximum plasma concentration (Cmax) and area under the time concentration curve (AUC0-24 hours) increases dose-proportionally over the approved recommended dosage range. Upon twice daily dosing, steady state conditions are achieved in approximately 7 days with an accumulation ratio of 1.4.

Absorption

Crinecerfont median time to reach Cmax (Tmax) is 4 hours following oral administration of CRENESSITY.

No clinically significant differences in crinecerfont Cmax or AUC were observed following administration of CRENESSITY oral capsules and oral solution.

Steady state exposures for crinecerfont in adults and pediatric patients following oral administration of CRENESSITY are presented in Table 6.

Table 6. Geometric Mean (CV%) for AUC 24,ss and Cmax in Adults and Pediatric Patients with Classic Congenital Adrenal Hyperplasia Following Oral Administration of CRENESSITY

Parameter | Geometric Mean (CV%)
 | Study 1 (adults) |  | Study 2 (pediatrics)
AUC24hr,ss (ng*h/mL) | Dose: 100 mg bid | 72846 (51%) | Dose 100 mg bid (≥ 55 kg) Dose 50 mg bid (≥ 20 to < 55 kg) | 74693 (48%) 47062 (51%)
Cmax (ng/mL) |  | 4231 (46%) | Dose 100 mg bid (≥ 55 kg) Dose 50 mg bid (≥ 20 to < 55 kg) | 4555 (43%) 2887 (48%)

CV%, coefficient of variation expressed as a percentage; bid, twice daily; steady-state exposure parameters are generated from simulation of 500 subjects based on population pharmacokinetic modeling and weight band appropriate formulation

Effect of Food

Following administration of CRENESSITY capsule, crinecerfont Cmax increased 4.9-fold and AUC increased 3.3-fold with a high-fat meal (800 to 1000 calories, 50% fat), compared to fasted conditions [see Dosage and Administration (2.2)].

Following administration of CRENESSITY oral solution, crinecerfont Cmax increased 8.6-fold and AUC increased 8.3-fold with a high-fat meal (800 to 1000 calories, 50% fat), compared to fasted conditions [see Dosage and Administration (2.2)]

Distribution

Mean apparent volume of distribution (CV%) of crinecerfont in adults with CAH is 852 L (31%). Crinecerfont plasma protein binding is greater than or equal to 99.9%.

Elimination

Crinecerfont’s effective half-life is approximately 14 hours with a mean (CV%) apparent clearance of 3.5 L/h (37%).

Metabolism

Crinecerfont is metabolized primarily by CYP3A4 and to a lesser extent by CYP2B6 in vitro. Additionally, CYP2C8 and CYP2C19 may also have minor contributions to crinecerfont metabolism.

Excretion

Following a single oral 100 mg dose of radiolabeled crinecerfont, approximately 47.3% (2.7% as unchanged) of the dose was recovered in feces and 2% (amount as unchanged is undetectable) in urine.

Specific Populations

No clinically significant differences in the pharmacokinetics of crinecerfont were observed based on age (range: 5 to 54 years), sex (58.7% male), race (4.8% Asian, 9.7% Black, 77.5% White), mild to severe hepatic impairment (Child Pugh Class A to C), or mild to moderate renal impairment (estimated glomerular filtration rate: equal to or greater than 44 mL/min/1.73 m^2; CKD-EPI 2009 formula for adults and bedside Schwartz formula for pediatric patients).

Crinecerfont has not been studied in patients with severe renal impairment or end-stage renal disease.

Drug Interaction Studies

Clinical Studies

Effect of Strong CYP3A4 Inducers on Crinecerfont: Crinecerfont Cmax decreased by 23% and AUC decreased by 62% following concomitant use with rifampin (strong CYP3A4 inducer) [see Dosage and Administration (2.3) and Drug Interactions (7.1)].

Effect of Strong CYP3A4 Inhibitors on Crinecerfont: Crinecerfont Cmax and AUC increased by 25% and 45%, respectively, when used concomitantly with ketoconazole (strong CYP3A4 inhibitor).

Effect of Crinecerfont on CYP3A Substrates: No clinically significant differences in the pharmacokinetics of midazolam (CYP3A4 substrate) were observed when co-administered with crinecerfont. Concomitant use of crinecerfont did not affect the pharmacokinetics of oral contraceptives containing ethinyl estradiol and levonorgestrel.

In Vitro Studies

Cytochrome P450 Enzymes: Crinecerfont does not inhibit CYP1A2, CYP2B6, CYP2C8, CYP2C9, CYP2C19, CYP2D6, and CYP2E1. Crinecerfont does not induce CYP2C8, CYP3A4, CYP1A2 and CYP2B6.

Transporter Systems: Crinecerfont does not inhibit P-glycoprotein (P-gp), breast cancer resistant protein (BCRP), bile salt export pump (BSEP), organic anion transporting polypeptide (OATP) 1B1, OATP1B3, organic anion transporter (OAT)1, OAT3, organic cation transporter (OCT)2, multidrug and toxin extrusion protein (MATE)1, or MATE2-K.

13 NONCLINICAL TOXICOLOGY

13.1 Carcinogenesis, Mutagenesis, Impairment of Fertility

Carcinogenesis

In a 2-year carcinogenicity study, rats were administered daily crinecerfont doses of 5, 15, and 100 mg/kg/day via oral gavage. An increased incidence of thyroid follicular cell combined adenomas and carcinomas was observed in female rats at the 100 mg/kg/day dose level (approximately 4-fold higher than human exposure at the MRHD based on AUC). Thyroid follicular cell tumors can occur in rats from excessive thyroid stimulating hormone (TSH) secondary to liver enzyme induction, which is not thought to commonly occur in humans. No evidence of increased tumorigenicity was seen in male rats up to approximately 5-fold higher than human exposure at the MRHD based on AUC or in female rats up to approximately 2-fold higher than human exposure at the MRHD based on AUC.

In a 6-month study in Tg.rasH2 mice, daily crinecerfont doses of 15, 50, 500, and 1500 mg/kg/day were administered via oral gavage. Crinecerfont did not increase the incidence of tumors in male or female transgenic mice (approximately 4-fold higher than human exposure at the MRHD based on AUC).

Mutagenesis

Crinecerfont was not mutagenic in the in vitro bacterial reverse mutation test (Ames) or clastogenic in the in vitro mammalian chromosomal aberrations assay in human peripheral blood lymphocytes or in the in vivo rat bone marrow micronucleus assay.

Impairment of Fertility

There were no crinecerfont-related effects on male or female fertility or female reproductive performance in rats treated orally with up to 1000 mg/kg/day crinecerfont at 2-fold higher than human exposure at the MRHD by AUC exposure.

14 CLINICAL STUDIES

14.1 Adults with Classic Congenital Adrenal Hyperplasia

The efficacy of CRENESSITY to reduce androgen levels and enable a reduced glucocorticoid dose while maintaining androgen control in adults with classic CAH was evaluated in a randomized, double-blind, placebo-controlled study (Study 1; NCT#04490915). This study enrolled 182 adults with classic CAH due to 21- hydroxylase deficiency on supraphysiological glucocorticoid doses and with androgen concentrations in the normal range or with inadequate androgen control.

Subjects were randomized to receive CRENESSITY 100 mg twice daily (N=122) or placebo (N=60) for 24 weeks. During the first 4 weeks of CRENESSITY treatment, subjects maintained a stable glucocorticoid regimen except for stress dosing as needed. During Weeks 4 to 12, the glucocorticoid dose was reduced as frequently as every 2 weeks without regard to androstenedione levels, with the goal to achieve a glucocorticoid dose of 8 to 10 mg/m^2/day in hydrocortisone dose equivalents adjusted for body surface area by Week 12. From Weeks 12 to 20, the glucocorticoid dose was further adjusted, if needed, to achieve androstenedione control by Week 24.

The mean (range) age was 31 (18 to 58) years, 51% were male, 90% were White, and 8% were Hispanic or Latino. At baseline, the mean (SD) glucocorticoid total daily dose in hydrocortisone equivalents was 32 (9) mg/day (18 [5] mg/m^2/day), with mean (SD) androstenedione levels of 620 (729) ng/dL prior to the morning glucocorticoid dose.

The efficacy of CRENESSITY was assessed by the least-squares (LS) mean (SEM) percent change from baseline in the total glucocorticoid daily dose while androstenedione was controlled (≤120% of baseline or ≤upper limit of normal [ULN]) after 24 weeks. The LS mean percent change from baseline in daily glucocorticoid dose was statistically significantly greater in the CRENESSITY group at -27% compared to -10% in the placebo group, as shown in Table 7.

Table 7: Primary Change From Baseline in Glucocorticoid Daily Dose While Maintaining Androstenedione Control at Week 24 in Adults with Classic Congenital Adrenal Hyperplasia (Study 1)

 | Treatment Group | Mean (SD) Baseline (mg/m^2/day) | LS Mean (SEM) Percent Change From Baseline (%) | Placebo-Subtracted LS Mean Difference (95% CI) (%)
Glucocorticoid Daily Dose* | CRENESSITY N=122 | 18 (5) | -27 (2) | -17 (-24, -10) p<0.0001
 | Placebo N=60 | 18 (6) | -10 (3)

CI=confidence interval; LS mean=least-squares mean; SD=standard deviation; SEM=standard error of the mean
* In hydrocortisone equivalents (4x equivalency factor for (methyl)predniso(lo)ne, 60x for dexamethasone) adjusted for body surface area.

At Week 24, there was a statistically significantly greater percentage of subjects achieving a reduction to a physiologic glucocorticoid daily dose (≤11 mg/m^2/day hydrocortisone equivalents) while androstenedione was controlled (≤120% of baseline or ≤ULN) with CRENESSITY compared to placebo (63% vs 18%, p<0.0001).

At Week 4, following a treatment period at a stable glucocorticoid dose regimen, the LS mean change from baseline in serum androstenedione in the CRENESSITY group was statistically significantly different at -299 ng/dL compared to the LS mean increase from baseline in the placebo group of 46 ng/dL, as shown in Table 8.

Table 8: Change From Baseline in Serum Androstenedione (ng/dL) at Week 4* in Adults with Classic Congenital Adrenal Hyperplasia (Study 1)

 | Treatment Group | Mean (SD) Baseline | LS Mean (SEM) Change from Baseline | Placebo-subtracted LS Mean Difference (95% CI)
Serum Androstenedione (ng/dL)† | CRENESSITY N=122 | 634 (796) | -299 (38) | -345 (-457, -232) p<0.0001
 | Placebo N=60 | 590 (572) | 46 (51)

CI=confidence interval; LS mean=least-squares mean; SD=standard deviation; SEM=standard error of the mean

* End of glucocorticoid stable period.

† Obtained prior to the morning glucocorticoid dose.

14.2 Pediatric Patients with Classic Congenital Adrenal Hyperplasia

The efficacy of CRENESSITY to improve androgen control and enable a reduced glucocorticoid dose while maintaining androgen control in pediatric patients with classic CAH was evaluated in a Phase 3 randomized, double-blind, placebo-controlled study (Study 2; NCT#04806451). This study enrolled 103 pediatric subjects 4 to 17 years of age with classic CAH due to 21-hydroxylase deficiency and inadequate androgen control on supraphysiological glucocorticoid doses.

Subjects were randomized to receive either CRENESSITY twice daily (N=69) or placebo (N=34) for 28 weeks, using weight-based dosing (50 mg twice daily via oral solution for subjects 20 to <55 kg [CRENESSITY N=37; placebo N=14 ], or 100 mg twice daily via oral capsules for subjects ≥55 kg [CRENESSITY N=32; placebo N=20]).

During the first 4 weeks of CRENESSITY treatment, subjects were maintained on a stable glucocorticoid regimen except for stress dosing, as needed. The primary efficacy endpoint was the change from baseline in serum androstenedione at Week 4. From Weeks 4 to 20, the glucocorticoid dose could be reduced as frequently as every 4 weeks provided androstenedione levels were controlled. The goal was to achieve a glucocorticoid dose of 8 to 10 mg/m^2/day (hydrocortisone dose equivalents adjusted for body surface area) by Week 28 while maintaining androstenedione control.

The mean (range) age was 12 (4 to 17) years, 41% were Tanner Stage 1 or 2, 52% were male, 63% were White, and 11% were Hispanic or Latino. With respect to concurrent glucocorticoid use at baseline, 92% of patients were receiving hydrocortisone alone and 8% were receiving prednisone [or equivalent] (with or without hydrocortisone). At baseline, subjects were receiving a mean (SD) glucocorticoid total daily dose in hydrocortisone equivalents of 16 (4) mg/m^2/day, and had a mean (SD) androstenedione level of 431 (461) ng/dL and mean (SD) serum 17-hydroxyprogesterone level of 8682 (6847) ng/dL prior to the morning glucocorticoid dose.

At Week 4, following a treatment period at a stable glucocorticoid dose regimen, the LS mean reduction from baseline in serum androstenedione in the CRENESSITY group was statistically significantly different at -197 ng/dL compared to the increase of 71 ng/dL in the placebo group, as shown in Table 9.

Table 9: Change From Baseline in Serum Androstenedione (ng/dL) at Week 4* in Pediatric Subjects with Classic Congenital Adrenal Hyperplasia (Study 2)

 | Treatment Group | Mean (SD) Baseline | LS Mean (SEM) Change from Baseline | Placebo-Subtracted LS Mean Difference (95% CI)
Serum Androstenedione (ng/dL) † | CRENESSITY N=69 | 405 (464) | -197 (40) | -268 (-403, -132) p=0.0002
 | Placebo N=34 | 483 (456) | 71 (56)

CI=confidence interval; LS mean=least-squares mean; SD=standard deviation; SEM=standard error of the mean

* End of glucocorticoid stable period.

†Obtained prior to the morning glucocorticoid dose.

At Week 4, following a treatment period at a stable glucocorticoid regimen, the LS mean reduction (SEM) from baseline in serum 17-hydroxyprogesterone in the CRENESSITY group was statistically significantly different at -5865 (572) ng/dL compared to the increase of 556 (818) ng/dL in the placebo group (LS Mean Treatment Difference -6421, 95% CI -8387, -4454, p<0.0001).

The LS mean percent change from baseline in the total glucocorticoid daily dose while androstenedione was controlled (≤120% of baseline or ≤ULN) at Week 28 in the CRENESSITY group was statistically significantly different at -18% compared to the increase of 6% in the placebo group, as shown in Table 10.

Table 10: Percent Change From Baseline in Glucocorticoid Daily Dose While Maintaining
Androstenedione Control at Week 28 in Pediatric Subjects with Classic Congenital Adrenal Hyperplasia (Study 2)

 | Treatment Group | Mean (SD) Baseline (mg/m^2/day) | LS Mean (SEM) Percent Change from Baseline (%) | Placebo-subtracted LS Mean Difference (95% CI) (%)
Glucocorticoid Daily Dose* | CRENESSITY N=69 | 17 (4) | -18 (2) | -24 (-30, -17) p<0.0001
 | Placebo N=34 | 16 (3) | 6 (3)

CI=confidence interval; LS mean=least-squares mean; SD=standard deviation; SEM=standard error of the mean;
*In hydrocortisone equivalents (4x equivalency factor for (methyl)predniso(lo)ne) adjusted for body surface area.

16 HOW SUPPLIED/STORAGE AND HANDLING

16.1 How Supplied

CRENESSITY Capsules

CRENESSITY (crinecerfont) capsules are available in the doses shown in Table 11.

Table 11. CRENESSITY Capsule Information

Capsule Strength | Capsule Color/Shape | Capsule Marking | Quantity in bottle | NDC Number
25 mg | Oval, orange soft gelatin capsules | Printed with ‘WWV 25’ in black ink | 60 | 70370-5025-1
50 mg | Oval, two-toned orange and gold soft gelatin capsules | Printed with ‘WWV 50’ in black ink | 60 | 70370-5050-1
100 mg | Oblong, gold soft gelatin capsules | Printed with ‘WWV 100’ in black ink | 30 | 70370-5100-1

CRENESSITY Oral Solution 50 mg/mL is a light yellow to orange, orange-flavored liquid. The amber polyethylene terephthalate (PET) bottle contains 30 mL oral solution (NBC 70370-5250-1).

16.2 Storage and Handling

CRENESSITY Capsules

Store at 15°C to 25°C (59°F to 77°F).

Packaged in child-resistant HDPE bottles. Do not freeze.

CRENESSITY Oral Solution

Store and dispense in original container. Store CRENESSITY Oral Solution in an upright position.

Store unopened bottles under refrigeration at 2°C to 8°C (36°F to 46°F). Do not freeze.

Once a bottle is opened for use, it may be stored under refrigeration at 2°C to 8°C (36°F to 46°F) or at room temperature (15°C to 25°C [59°F to 77°F]) for up to 30 days. Discard any unused oral solution after 30 days of first opening the bottle.

Packaged in child-resistant PET bottles.

17 PATIENT COUNSELING INFORMATION

Advise the patients and/or caregivers to read the FDA-approved patient labeling (Patient Information leaflet and CRENESSITY oral solution IFU, if applicable).

Administration Information

Counsel patients that CRENESSITY must be taken with a meal, without regard to fat or caloric content [see Dosage and Administration (2.2) and Clinical Pharmacology (12.3)].

Drug Interactions

Inform patients that the CRENESSITY dosage will need to be increased if they are taking strong or moderate CYP3A4 inducers [see Dosage and Administration (2.3, 2.4), Drug Interactions (7.1)].

Hypersensitivity Reactions

Advise patients to seek prompt medical attention if signs or symptoms of hypersensitivity reactions occur. Advise patients who have had signs or symptoms of systemic hypersensitivity reactions to CRENESSITY that they should not receive CRENESSITY [see Contraindications (4) and Warnings and Precautions (5.1)].

Acute Adrenal Insufficiency or Adrenal Crisis with Inadequate Concomitant Glucocorticoid Therapy

Inform patients that they should continue glucocorticoids when taking CRENESSITY. Counsel patients that any adjustment of glucocorticoid doses should be done under the guidance of their health care provider. Counsel patients about the continued need for stress dose glucocorticoids during times of increased cortisol need (e.g., during illness) [see Warnings and Precautions (5.2)].

Pregnancy

Advise women who are exposed to CRENESSITY during pregnancy that there is a pregnancy safety study [see Use in Specific Populations (8.1)].

For information on CRENESSITY, visit www.CRENESSITY.com or call 1-855-CRNSITY
(1-855-276-7489).

Distributed by: Neurocrine Biosciences, Inc., San Diego, CA 92130, U.S.A.

CRENESSITY is a trademark of Neurocrine Biosciences, Inc.

PATIENT INFORMATION
CRENESSITY® (kreh NEH sih tee)
(CRINECERFONT)
CAPSULES AND ORAL SOLUTION

What is CRENESSITY?
CRENESSITY is a prescription medicine used together with glucocorticoids (steroids) to control androgen (testosterone-like hormone) levels in adults and children 4 years of age and older with classic congenital adrenal hyperplasia (CAH).
It is not known if CRENESSITY is safe and effective in children younger than 4 years of age.

Do not take CRENESSITY if you:

- are allergic to crinecerfont, or any of the ingredients in CRENESSITY. See the end of this Patient Information leaflet for a complete list of ingredients in CRENESSITY.

Before taking CRENESSITY, tell your health care provider about all of your medical conditions, including if you:

- are pregnant or plan to become pregnant. It is not known if CRENESSITY will harm your unborn baby. If you become pregnant while taking CRENESSITY, tell your health care provider right away. There is a pregnancy safety study for women who become pregnant during treatment with CRENESSITY.
- are breastfeeding or plan to breastfeed. It is not known if CRENESSITY passes into your breast milk. Talk to your health care provider about the best way to feed your baby during treatment with CRENESSITY.

Tell your healthcare provider about all the medicines you take, including prescription and over-the-counter medicines, vitamins and herbal supplements.
Taking CRENESSITY with certain other medicines may cause your CRENESSITY to not work as well. Do not start any new medicines while taking CRENESSITY without talking to your health care provider first.

How should I take CRENESSITY?

- Take CRENESSITY exactly as your health care provider tells you to. Your health care provider will tell you how much CRENESSITY to take and when to take it.
- Do not stop taking CRENESSITY without talking to your health care provider first.
- While your health care provider may lower your glucocorticoids (steroids), you should continue to take glucocorticoids (steroids) to treat adrenal insufficiency, including stress dose steroids (such as when your body may be under stress from fever, infection or surgery). Do not change your daily glucocorticoid (steroid) dose without talking to your health care provider. See “What are the possible side effects of CRENESSITY?”
- Take CRENESSITY by mouth 2 times each day, in the morning and evening with a meal.
- Swallow CRENESSITY capsules whole with liquid. Tell your health care provider if you cannot swallow the capsule whole. Your healthcare provider may need to switch you to CRENESSITY oral solution.
- If your health care provider prescribes CRENESSITY oral solution, you should use the oral dosing syringe that your pharmacist will give you to measure and take the correct dose. See the Instructions for Use for CRENESSITY oral solution for more information.
- If you miss a dose of CRENESSITY, take it as soon as you remember (even if it is almost time for your next dose). Take the next dose at your regular time.

What are the possible side effects of CRENESSITY?
CRENESSITY may cause serious side effects, including:

- Allergic reactions. Symptoms of an allergic reaction include tightness of the throat, trouble breathing or swallowing, swelling of the lips, tongue, or face, and rash. If you have an allergic reaction to CRENESSITY, get emergency medical help right away and stop taking CRENESSITY.
- Risk of Sudden Adrenal Insufficiency or Adrenal Crisis with Too Little Glucocorticoid (Steroid) Medicine. Sudden adrenal insufficiency or adrenal crisis can happen in people with congenital adrenal hyperplasia who are not taking enough glucocorticoid (steroid) medicine. You should continue taking your glucocorticoid (steroid) medicine during treatment with CRENESSITY. Certain conditions such as infection, severe injury, or shock may increase your risk for sudden adrenal insufficiency or adrenal crisis. Tell your health care provider if you get a severe injury, infection, illness, or have any planned surgery during treatment with CRENESSITY. Your health care provider may need to change your dose of glucocorticoid (steroid) medicine.

The most common side effects of CRENESSITY in adults include:

• tiredness

• back pain

• headache

• decreased appetite

• dizziness

• muscle pain

• joint pain

The most common side effects of CRENESSITY in children include:

• headache

• nasal congestion

• stomach pain

• nose bleeds

• tiredness

These are not all the possible side effects of CRENESSITY. Call your doctor for medical advice about side effects. You may report side effects to FDA at 1-800-FDA-1088.

How should I store CRENESSITY?

- Store CRENESSITY capsules at room temperature between 59°F to 77°F (15°C to 25°C). Do not freeze.
- Store unopened CRENESSITY oral solution refrigerated between 36° to 46°F (2° to 8°C). Do not freeze.
  - Store in the original container in an upright position.
  - After opening the bottle, CRENESSITY oral solution may be stored in the refrigerator or at room temperature between 59°F to 77°F (15°C to 25°C) for up to 30 days.
  - Use CRENESSITY oral solution within 30 days of first opening the bottle. Throw away (disopose of) any unused medicine after 30 days.

Keep CRENESSITY and all medicines out of the reach of children.

General information about the safe and effective use of CRENESSITY.
Medicines are sometimes prescribed for purposes other than those listed in a Patient Information leaflet. Do not use CRENESSITY for a condition for which it was not prescribed. Do not give CRENESSITY to other people, even if they have the same symptoms that you have. It may harm them. You can ask your pharmacist or health care provider for information about CRENESSITY that is written for health professionals.

What are the ingredients in CRENESSITY?
Active ingredient: crinecerfont
Inactive ingredients:

- CRENESSITY capsules: lauroyl polyoxyl-32 glycerides, medium chain triglycerides, propylene glycol dicaprylate/dicaprate, and Vitamin E polyethylene glycol succinate. The capsule shell contains gelatin, glycerin, red iron oxide, Sorbitol glycerin blend, titanium dioxide, yellow iron oxide.
- CRENESSITY oral solution: butylated hydroxytoluene, medium-chain triglycerides, oleoyl polyoxyl glycerides, orange flavor, and saccharin.

Distributed by: Neurocrine Biosciences, Inc., San Diego, CA 92130, U.S.A
For more information, go to www.CRENESSITY.com or call 1-855-CRNSITY (1 855-276-7489).

This Patient Information has been approved by the U.S. Food and Drug Administration Issued: 12/2024

INSTRUCTIONS FOR USE

CRENESSITYTM (kreh NEH sih tee)

(crinecerfont)

oral solution

50 mg/mL

Read this Instructions for Use for important information you need to know before taking CRENESSITY oral solution for the first time and each time you get a refill. There may be new information. This information does not take the place of talking to your health care provider about your medical condition or treatment.

Important information:

- Take CRENESSITY oral solution exactly as your health care provider tells you to. Your health care provider will tell you how much CRENESSITY oral solution to take and when to take it.
- CRENESSITY oral solution should be taken with a meal in the morning and evening.
- Always use the oral syringe provided by your pharmacist to make sure you measure the right amount of CRENESSITY oral solution.
- Use CRENESSITY oral solution within 30 days of first opening the bottle. After 30 days of first opening the bottle, throw away (dispose of) any CRENESSITY oral solution that has not been used.
- Do not stop taking CRENESSITY oral solution without talking to your health care provider first.
- See the Patient Information Leaflet that comes with CRENESSITY for more information.

Supplies not included in the package:

- Press-in bottle adapter
- Oral syringes

You must get a press-in bottle adapter and oral syringe from your pharmacist. Your pharmacist can help you choose the right press-in bottle adapter and oral syringes to use with CRENESSITY oral solution.

Call your pharmacist right away if you do not have a press-in bottle adapter and the right oral syringe to use with your CRENESSITY oral solution.

How should I prepare and take CRENESSITY oral solution?

1. Gather the supplies (see Figure A):
• CRENESSITY oral solution bottle
• Press-in bottle adapter
• Oral syringe

Figure A

2. Inspect CRENESSITY.

1. Check the pharmacy label to make sure the medicine name and dose are correct.
2. Check the oral solution bottle, oral syringe, and press-in bottle adapter for signs of damage.

Do not use CRENESSITY oral solution bottle, oral syringe, or press-in bottle adapter if it appears to be damaged or tampered with. Contact your pharmacist or health care provided.

3. Prepare CRENESSITY oral solution.
a. Remove the child-resistant cap by pressing it down while twisting it to the left (counterclockwise) (See Figure B).
b. Carefully puncture and peel off the seal from the bottle (See Figure C).
c. First time use of the bottle only. While holding the bottle firmly with one hand, use the thumb on your other hand to push the press-in bottle adapter into the bottle as far as it will go using constant pressure (see Figure D).
Do not remove the press-in bottle adapter after it has been inserted.

Figure B
Figure C
Figure D

4. Prepare the dose.
a. Push in the plunger of the oral syringe as far as it will go (see Figure E).
If the oral syringe comes with a cap, pull off the syringe cap.

Figure E

b. Insert the tip of the oral syringe into the press-in bottle adapter, then with the oral syringe still inserted, turn the bottle upside down (see Figure F).

Figure F

c. Slowly pull the plunger of the oral syringe until the part of the plunger that is touching the liquid is even with the marking of your prescribed dose (see Figure G).
Note: Slowly push the plunger to return any large air bubbles back to the bottle and repeat the prior step until the air bubbles are gone.

Figure G

d. When you have measured the correct amount of CRENESSITY, keep the oral syringe inserted in the bottle and turn the bottle and oral syringe right side up. Hold the oral syringe from the middle, then carefully remove it from the bottle (see Figure H).
Do not touch the plunger to avoid oral solution accidentally coming out of the syringe before you are ready to give the medicine.

Figure H

5. Give a dose of CRENESSITY oral solution.
a. Place the tip of the oral syringe inside your mouth and point it towards the inside of the cheek.
b. Slowly push the plunger all the way down to give the full dose (see Figure I).
c. Put the child-resistant cap back on the bottle with the press-in bottle adapter still inserted by turning the cap to the right (clockwise).
Do not remove the press-in bottle adapter. The child-resistant cap will fit over it.

Figure I

6.Rinse and store the oral syringe.
a. Remove the plunger from the oral syringe.
b. Rinse both parts with water (see Figure J).
c. Push plunger back into the oral syringe to remove any large droplets of water.
d. Remove the plunger from the oral syringe and allow these separated parts to air dry thoroughly on a clean surface.
e. Push the dried plunger back into the dried oral syringe.
f. Store the oral syringe in a clean, dry place.

Figure J

How should I store CRENESSITY oral solution?

- Store CRENESSITY oral solution in the original container in an upright position.
- Store the unopened CRENESSITY oral solution bottle in the refrigerator at 36°F to 46°F (2°C to 8°C (2°C to 8°C). Do not freeze.
- After opening the bottle, CRENESSITY oral solution can be stored in the refrigerator or at room temperature between 59°F to 77°F (15°C to 25°C) for up to 30 days.
- Use CRENESSITY oral solution within 30 days of first opening the bottle. Throw away (dispose of) any unused medicine after 30 days.
- Keep CRENESSITY oral solution and all medicines out of the reach of children.

Distributed by: Neurocrine Biosciences, Inc., San Diego, CA 92130, U.S.A
For information, visit www.CRENESSITY.com or call 1-855-CRNSITY (1 855-276-7489).

This Instructions for Use has been approved by the U.S. Food and Drug Administration.

Issued: 12/2024

PACKAGE LABEL

PRINCIPAL DISPLAY PANEL

NDC 70370-5025-1
Crenessity
(crinecerfont) capsules
25 mg
60 Capsules
Rx only

PACKAGE LABEL

PRINCIPAL DISPLAY PANEL

NDC 70370-5050-1
Crenessity
(crinecerfont) capsules
50 mg
60 Capsules
Rx only

PACKAGE LABEL

PRINCIPAL DISPLAY PANEL

NDC 70370-5100-1
Crenessity
(crinecerfont) capsules
100 mg
30 Capsules
Rx only

PACKAGE LABEL

PRINCIPAL DISPLAY PANEL

NDC 70370-5250-1
Crenessity
(crinecerfont) oral solution
50 mg/mL
30 mL
Rx only